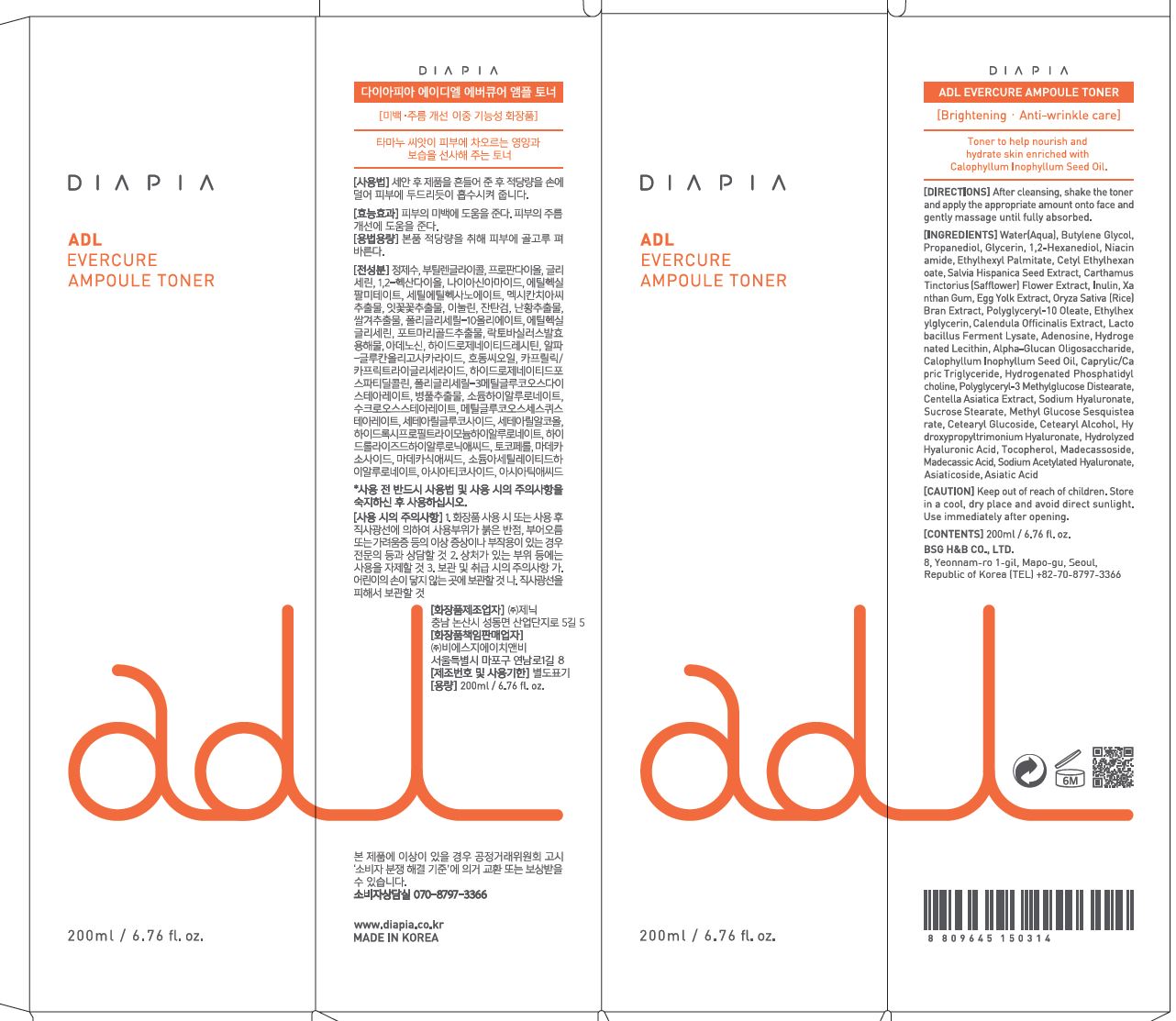 DRUG LABEL: DIAPIA ADL Evercure Ampoule Toner
NDC: 71857-0017 | Form: LIQUID
Manufacturer: BSG H & B Co., Ltd.
Category: otc | Type: HUMAN OTC DRUG LABEL
Date: 20211201

ACTIVE INGREDIENTS: ADENOSINE 0.04 g/100 mL; NIACINAMIDE 2 g/100 mL
INACTIVE INGREDIENTS: WATER

Drug Facts

ACTIVE INGREDIENT

Niacinamide

INACTIVE INGREDIENT

Water(Aqua)
Butylene Glycol
Propanediol
Glycerin
1,2-Hexanediol
Glycerin
Water(Aqua)
Ethylhexyl Palmitate
Cetyl Ethylhexanoate
Polyglyceryl-10 Oleate
Hydrogenated Lecithin
Inulin
Alpha-Glucan Oligosaccharide
Oryza Sativa (Rice) Bran Extract
Water(Aqua)
Butylene Glycol
1,2-Hexanediol
Water(Aqua)
1,2-Hexanediol
Sodium Hyaluronate
Hydroxypropyltrimonium Hyaluronate
Hydrolyzed Hyaluronic Acid
Sodium Acetylated Hyaluronate
Egg Yolk Extract
Water(Aqua)
Butylene Glycol
1,2-Hexanediol
Calendula Officinalis Extract
Lactobacillus Ferment Lysate
Water(Aqua)
Glycerin
Butylene Glycol
1,2-Hexanediol
Carthamus Tinctorius (Safflower) Flower Extract
Water(Aqua)
1,2-Hexanediol
Water(Aqua)
Glycerin
Butylene Glycol
1,2-Hexanediol
Caprylic/Capric Triglyceride
Hydrogenated Phosphatidylcholine
Centella Asiatica Extract
Sucrose Stearate
Cetearyl Alcohol
Madecassoside
Madecassic Acid
Asiaticoside
Asiatic Acid
Salvia Hispanica Seed Extract
Water(Aqua)
1,2-Hexanediol
Glycerin
Water(Aqua)
Calophyllum Inophyllum Seed Oil
1,2-Hexanediol
Polyglyceryl-3 Methylglucose Distearate
Butylene Glycol
Methyl Glucose Sesquistearate
Cetearyl Glucoside
Xanthan Gum
Ethylhexylglycerin
Tocopherol

PURPOSE

Brightening, anti wrinkle care

keep out of reach of the children

INDICATIONS AND USAGE

apply an appropriate amount onto face and gently massage until fully absorbed

WARNINGS

1.Keep out of reach of children.

2.Store in a cool, dry place and avoid direct sunlight.

3.If abnormal symptoms occur after use, stop use and consult with a skin specialist.

DOSAGE AND ADMINISTRATION

for external use only